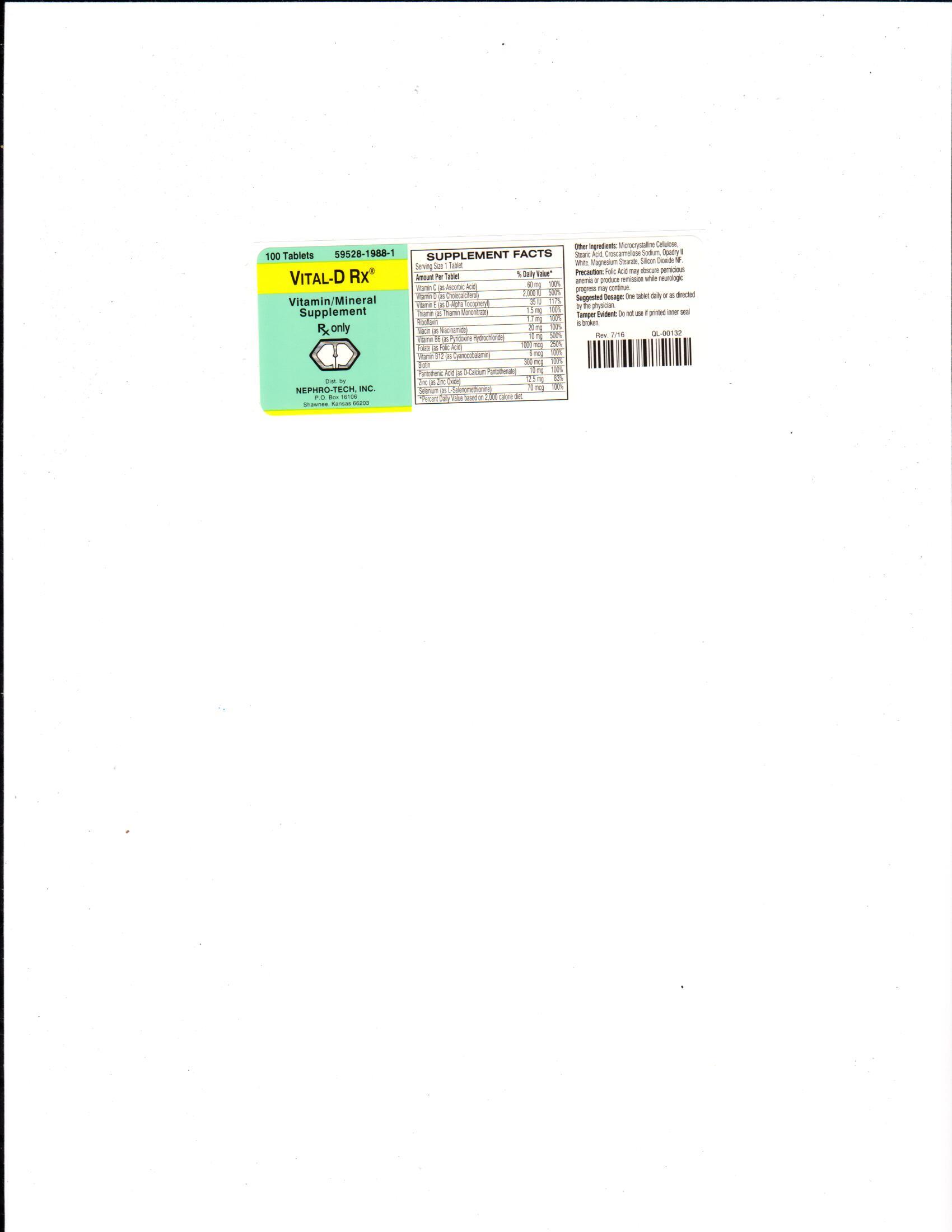 DRUG LABEL: Vital-D Rx
NDC: 59528-1988 | Form: TABLET, COATED
Manufacturer: Nephro-Tech, Inc.
Category: prescription | Type: HUMAN PRESCRIPTION DRUG LABEL
Date: 20210714

ACTIVE INGREDIENTS: ASCORBIC ACID 60 mg/1 1; CHOLECALCIFEROL 2000 [iU]/1 1; TOCOPHEROL 35 [iU]/1 1; THIAMINE 1.5 mg/1 1; RIBOFLAVIN 1.7 mg/1 1; NIACINAMIDE 20 mg/1 1; PYRIDOXINE HYDROCHLORIDE 10 mg/1 1; FOLIC ACID 1 mg/1 1; COBALAMIN 6 ug/1 1; BIOTIN 300 ug/1 1; PANTOTHENIC ACID 10 mg/1 1; ZINC OXIDE 12.5 mg/1 1; SELENOMETHIONINE 70 ug/1 1

Vital-D Rx (ascorbic acid, cholecalciferol, d-alpha tocopheryl, thiamin mononitrate, riboflavin, niacinamide, pyridoxine hydrochloride, folic acid, cyanocobalamin, biotin, pantothenic acid, zinc and selenium)

Description

Vital-D Rx is a prescription folic acid supplement with additional nutrients for kidney dialysis patients. Vital-D Rx is a white, film-coated, oval shaped tablet.

Suggested Dosage

One tablet daily or as directed by the physician.

Precaution

Folic Acid may obscure pernicious anemia or produce remission while neurologic progress may continue.

Package Label/Principal Display Panel

59528-1988-1

Rx Only

Vital-D Rx

Vitamin/Mineral Supplement

100 tablets